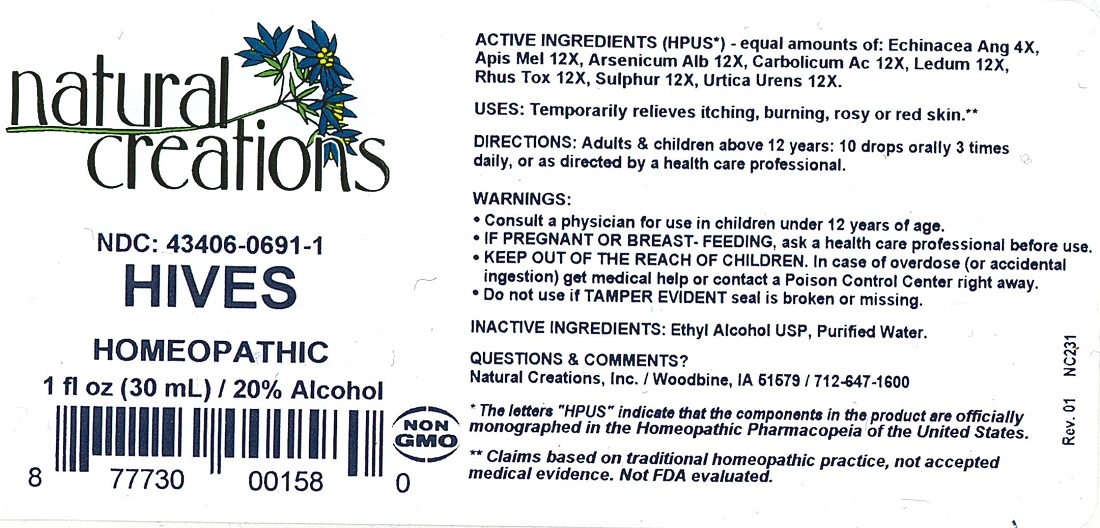 DRUG LABEL: Hives
NDC: 43406-0691 | Form: LIQUID
Manufacturer: Natural Creations, Inc
Category: homeopathic | Type: HUMAN OTC DRUG LABEL
Date: 20251216

ACTIVE INGREDIENTS: ECHINACEA ANGUSTIFOLIA WHOLE 4 [hp_X]/1 mL; APIS MELLIFERA 12 [hp_X]/1 mL; ARSENIC TRIOXIDE 12 [hp_X]/1 mL; PHENOL 12 [hp_X]/1 mL; RHODODENDRON TOMENTOSUM LEAFY TWIG 12 [hp_X]/1 mL; TOXICODENDRON PUBESCENS LEAF 12 [hp_X]/1 mL; SULFUR 12 [hp_X]/1 mL; URTICA URENS WHOLE 12 [hp_X]/1 mL
INACTIVE INGREDIENTS: ALCOHOL; WATER

Hives

ACTIVE INGREDIENT

ACTIVE INGREDIENTS (*HPUS) - equal amounts of: Echinacea Ang 4X, Apis Mel 12X, Arsenicum Alb 12X, Carbolicum Ac 12X, Ledum 12X, Rhus Tox 12X, Sulphur 12X, Urtica Urens 12X

INDICATIONS AND USAGE

USES: Temporarily relieves itching, burning, rosy or red skin.**

PURPOSE

USES: Temporarily relieves itching, burning, rosy or red skin.**

DOSAGE AND ADMINISTRATION

DIRECTIONS: Adults & children above 12 years: 10 drops orally 3 times daily, or as directed by a health care professional.

KEEP OUT OF REACH OF CHILDREN

KEEP OUT OF THE REACH OF CHILDREN. In case of overdose (or accidental ingestion) get medical help or contact a Poison Control Center right away.

WARNINGS:

- Consult a physician for use in children under 12 years of age.
- IF PREGNANT OR BREAST-FEEDING, ask a health care professional before use.
- KEEP OUT OF THE REACH OF CHILDREN. In case of overdose (or accidental ingestion) get medical help or contact a Poison Control Center right away.
- Do not use if TAMPER EVIDENT seal is broken or missing.

INACTIVE INGREDIENTS: Ethyl Alcohol USP, Purified Water

QUESTIONS & COMMENTS?

Natural Creations, Inc. / Woodbine, IA 51579 / 712-647-1600

REFERENCES

*The letters "HPUS" indicate the components in the product are officially monographed in the Homeopathic Pharmacopeia of the United States.

**Claims based on traditional homeopathic practice, not accepted medical evidence. Not FDA evaluated.

PACKAGE LABEL

NDC:43406-0691-1

Hives

HOMEOPATHIC

1 fl oz (30mL) / 20% Alcohol